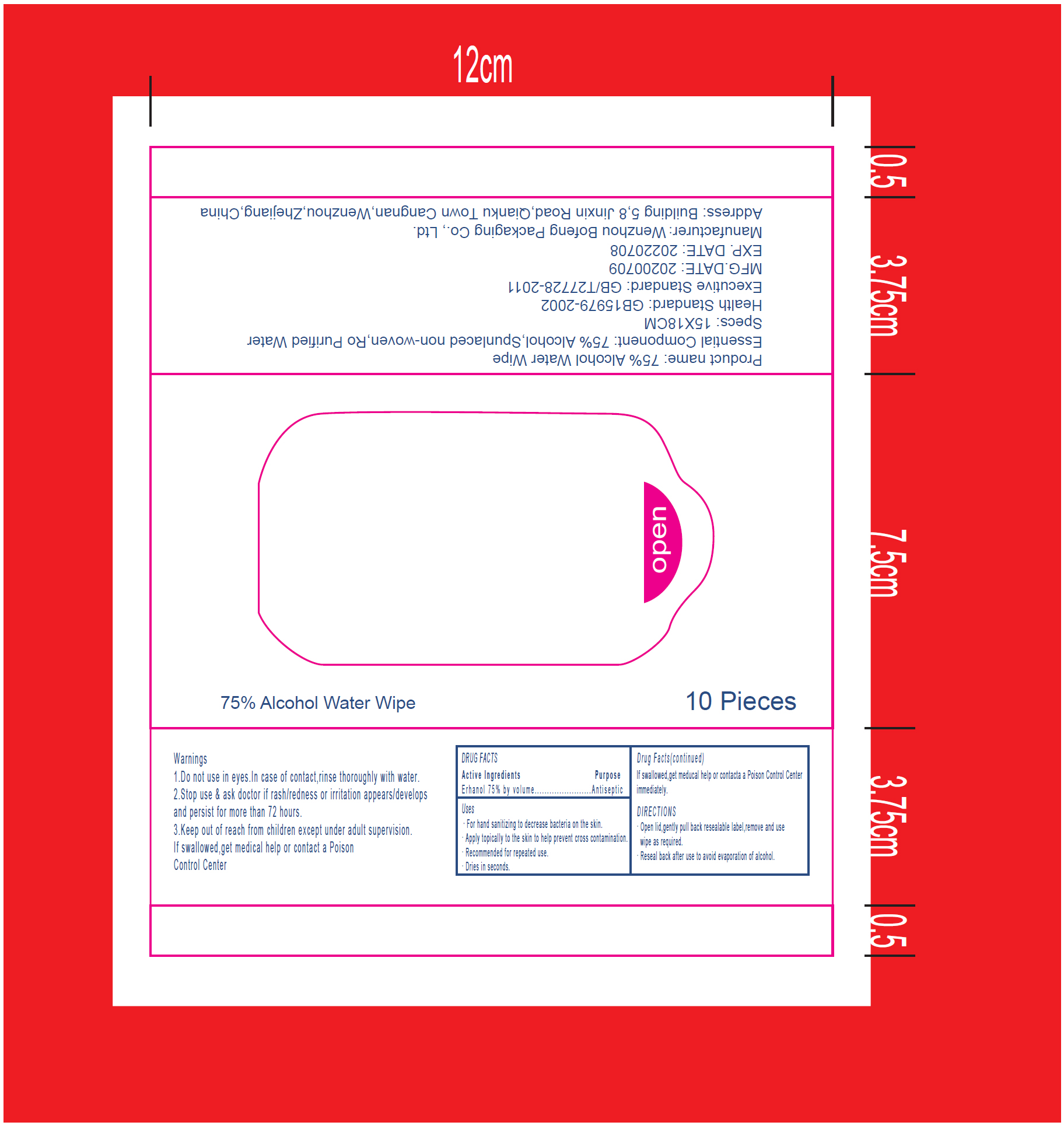 DRUG LABEL: Alcohol wipes
NDC: 79014-002 | Form: CLOTH
Manufacturer: Wenzhou Bofeng Packaging Co., Ltd.
Category: otc | Type: HUMAN OTC DRUG LABEL
Date: 20200716

ACTIVE INGREDIENTS: ALCOHOL 75 mL/100 g
INACTIVE INGREDIENTS: WATER

75% Alcohol water wipes

Active Ingredient(s)

Alcohol 75%. Purpose: Antiseptic

Purpose

Antiseptic

Use

- For hand sanitizing to decrease bacteria on the skin.
- Apply topically to the skin to help prevent cross contamination.
- Recommended for repeated use.
- Dries in seconds.

Warnings

If swallowed, get medical help or contact a poison control center immediately

Do not use in eyes. In case of contact, rinse thoroughly with water.

Stop use and ask doctor if rash/redness or irritation appears/develops and persist for more than 72 hours.

Keep out of reach of children except under adult supervision. If swallowed, get medical help or contact a poison control center

Directions

- Open lid, gently pull back resealable label, remove and use wipe as required.
- Reseal back after use to avoid evaporation of alcohol.

Inactive ingredients

water

Package Label - Principal Display Panel

79014-002-02 10PCS